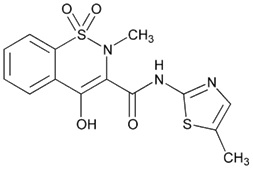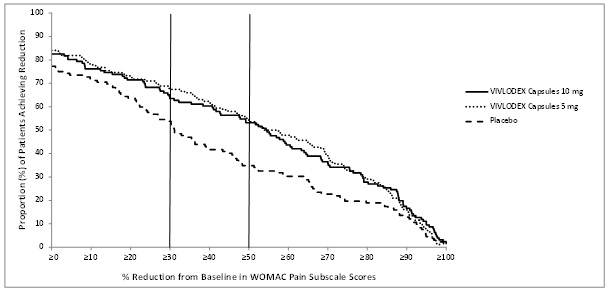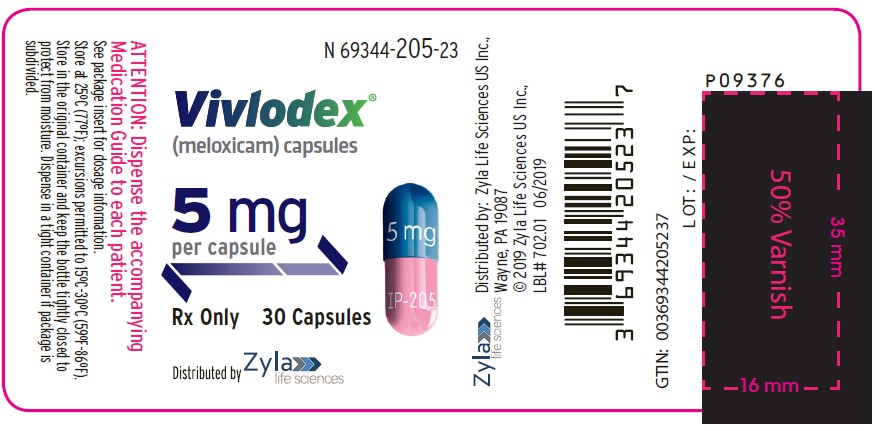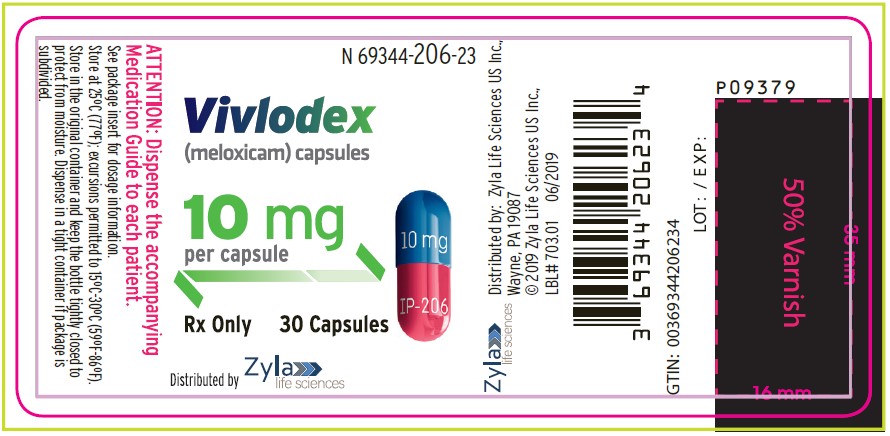 DRUG LABEL: Vivlodex
NDC: 69344-205 | Form: CAPSULE
Manufacturer: Egalet US Inc.
Category: prescription | Type: HUMAN PRESCRIPTION DRUG LABEL
Date: 20210430

ACTIVE INGREDIENTS: MELOXICAM 5 mg/1 1
INACTIVE INGREDIENTS: LACTOSE MONOHYDRATE; SODIUM LAURYL SULFATE; MICROCRYSTALLINE CELLULOSE; CROSCARMELLOSE SODIUM; SODIUM STEARYL FUMARATE; GELATIN, UNSPECIFIED; TITANIUM DIOXIDE; FD&C BLUE NO. 2; PIGMENT RED 5

HIGHLIGHTS OF PRESCRIBING INFORMATION

These highlights do not include all the information needed to use VIVLODEX™ safely and effectively. See full prescribing information for VIVLODEX.
VIVLODEX (meloxicam) capsules, for oral use
Initial U.S. Approval: 2000

WARNING: RISK OF SERIOUS CARDIOVASCULAR AND GASTROINTESTINAL EVENTS

See full prescribing information for complete boxed warning.

- Nonsteroidal anti-inflammatory drugs (NSAIDs) cause an increased risk of serious cardiovascular thrombotic events, including myocardial infarction and stroke, which can be fatal. This risk may occur early in treatment and may increase with duration of use. (5.1)
- VIVLODEX is contraindicated in the setting of coronary artery bypass graft (CABG) surgery. (4, 5.1)
- NSAIDs cause an increased risk of serious gastrointestinal (GI) adverse events including bleeding, ulceration, and perforation of the stomach or intestines, which can be fatal. These events can occur at any time during use and without warning symptoms. Elderly patients and patients with a prior history of peptic ulcer disease and/or GI bleeding are at greater risk for serious GI events. (5.2)

RECENT MAJOR CHANGES

Warnings and Precautions, Drug Reaction with Eosinophilia and Systemic Symptoms (DRESS) (5.10) 04/2021
Warnings and Precautions, Fetal Toxicity (5.11) 04/2021

1 INDICATIONS AND USAGE

VIVLODEX is a non-steroidal anti-inflammatory drug indicated for management of osteoarthritis (OA) pain. (1)

2 DOSAGE AND ADMINISTRATION

- Start with 5 mg orally once daily. May increase dose to 10 mg in patients who require additional analgesia (2.1)
- Use the lowest effective dose for shortest duration consistent with individual patient treatment goals (2.1)
- VIVLODEX capsules are not interchangeable with other formulations of oral meloxicam even if the milligram strength is the same. (2.2)

3 DOSAGE FORMS AND STRENGTHS

VIVLODEX (meloxicam) Capsules: 5 mg or 10 mg (3)

4 CONTRAINDICATIONS

- Known hypersensitivity to meloxicam or any components of the drug product (4)
- History of asthma, urticaria, or other allergic-type reactions after taking aspirin or other NSAIDs (4)
- In the setting of CABG surgery (4)

5 WARNINGS AND PRECAUTIONS

- Hepatotoxicity: Inform patients of warning signs and symptoms of hepatotoxicity. Discontinue if abnormal liver tests persist or worsen or if clinical signs and symptoms of liver disease develop (5.3)
- Hypertension: Patients taking some antihypertensive medications may have impaired response to these therapies when taking NSAIDs. Monitor blood pressure (5.4, 7)
- Heart Failure and Edema: Avoid use of VIVLODEX in patients with severe heart failure unless benefits are expected to outweigh risk of worsening heart failure (5.5)
- Renal Toxicity: Monitor renal function in patients with renal or hepatic impairment, heart failure, dehydration, or hypovolemia. Avoid use of VIVLODEX in patients with advanced renal disease unless benefits are expected to outweigh risk of worsening renal function (5.6)
- Anaphylactic Reactions: Seek emergency help if an anaphylactic reaction occurs (5.7)
- Exacerbation of Asthma Related to Aspirin Sensitivity: VIVLODEX is contraindicated in patients with aspirin-sensitive asthma. Monitor patients with preexisting asthma (without aspirin sensitivity) (5.8)
- Serious Skin Reactions: Discontinue VIVLODEX at first appearance of skin rash or other signs of hypersensitivity (5.9)
- Drug Reaction with Eosinophilia and Systemic Symptoms (DRESS): Discontinue and evaluate clinically (5.10)
- Fetal Toxicity: Limit use of NSAIDs, including VIVLODEX, between about 20 to 30 weeks in pregnancy due to the risk of oligohydramnios/fetal renal dysfunction. Avoid use of NSAIDs in women at about 30 weeks gestation and later in pregnancy due to the risks of oligohydramnios/fetal dysfunction and premature closure of the fetal ductus arteriosus (5.11, 8.1)
- Hematologic Toxicity: Monitor hemoglobin or hematocrit in patients with any signs or symptoms of anemia (5.12, 7)

6 ADVERSE REACTIONS

Most common adverse reactions (incidence ≥2% in controlled clinical trials of VIVLODEX 5 mg or 10 mg group) are diarrhea, nausea, abdominal discomfort. (6.1)

To report SUSPECTED ADVERSE REACTIONS, contact Egalet US Inc., at 1-800-518-1084 or FDA at 1-800-FDA-1088 or www.fda.gov/medwatch.

7 DRUG INTERACTIONS

- Drugs that Interfere with Hemostasis (e.g. warfarin, aspirin, SSRIs/SNRIs): Monitor patients for bleeding who are concomitantly taking VIVLODEX with drugs that interfere with hemostasis. Concomitant use of VIVLODEX and analgesic doses of aspirin is not generally recommended (7)
- ACE inhibitors, Angiotensin Receptor Blockers (ARB), or Beta-Blockers: Concomitant use with VIVLODEX may diminish the antihypertensive effect of these drugs. Monitor blood pressure (7)
- ACE Inhibitors and ARBs: Concomitant use with VIVLODEX in elderly, volume depleted, or those with renal impairment may result in deterioration of renal function. In such high risk patients, monitor for signs of worsening renal function (7)
- Diuretics: NSAIDs can reduce natriuretic effect of furosemide and thiazide diuretics. Monitor patients to assure diuretic efficacy including antihypertensive effects (7)
- Digoxin: Concomitant use with VIVLODEX can increase serum concentration and prolong half-life of digoxin. Monitor serum digoxin levels (7)

8 USE IN SPECIFIC POPULATIONS

- Pregnancy: Use of NSAIDs during the third trimester of pregnancy increases the risk of premature closure of the fetal ductus arteriosus. Avoid use of NSAIDs in pregnant women starting at 30 weeks gestation (5.10, 8.1)
- Infertility: NSAIDs are associated with reversible infertility. Consider withdrawal of VIVLODEX in women who have difficulties conceiving (8.3)

FULL PRESCRIBING INFORMATION

WARNING: RISK OF SERIOUS CARDIOVASCULAR AND GASTROINTESTINAL EVENTS

Cardiovascular Thrombotic Events

- Nonsteroidal anti-inflammatory drugs (NSAIDs) cause an increased risk of serious cardiovascular thrombotic events, including myocardial infarction and stroke, which can be fatal. This risk may occur early in treatment and may increase with duration of use [see Warnings and Precautions (5.1)].
- VIVLODEX is contraindicated in the setting of coronary artery bypass graft (CABG) surgery [see Contraindications (4), Warnings and Precautions (5.1)].

Gastrointestinal Bleeding, Ulceration, and Perforation

- NSAIDs cause an increased risk of serious gastrointestinal (GI) adverse events including bleeding, ulceration, and perforation of the stomach or intestines, which can be fatal. These events can occur at any time during use and without warning symptoms. Elderly patients and patients with a prior history of peptic ulcer disease and/or GI bleeding are at greater risk for serious GI events [see Warnings and Precautions (5.2)].

1 INDICATIONS AND USAGE

VIVLODEX is indicated for management of osteoarthritis pain.

2 DOSAGE AND ADMINISTRATION

2.1 Dosage

Use the lowest effective dosage for the shortest duration consistent with individual patient treatment goals [see Warnings and Precautions (5)].

For management of osteoarthritis pain, the recommended starting dosage is 5 mg orally once daily. Dose may be increased to 10 mg in patients who require additional analgesia. The maximum recommended daily oral dose of VIVLODEX is 10 mg.

In patients on hemodialysis, the maximum daily dosage is 5 mg [see Warnings and Precautions (5.6), Use in Specific Populations (8.7), Clinical Pharmacology (12.3)]

2.2 Non-Interchangeability with Other Formulations of Meloxicam

VIVLODEX capsules have not shown equivalent systemic exposure to other formulations of oral meloxicam. Therefore, VIVLODEX capsules are not interchangeable with other formulations of oral meloxicam even if the total milligram strength is the same. Do not substitute similar dose strengths of other meloxicam products [see Clinical Pharmacology (12.3)].

3 DOSAGE FORMS AND STRENGTHS

VIVLODEX (meloxicam) capsules: 5 mg – light pink body with a dark blue cap (imprinted IP-205 on the body and 5 mg on the cap in white ink).

VIVLODEX (meloxicam) capsules: 10 mg – pink body and a dark blue cap (imprinted IP-206 on the body and 10 mg on the cap in white ink).

4 CONTRAINDICATIONS

VIVLODEX is contraindicated in the following patients:

- Known hypersensitivity (e.g., anaphylactic reactions and serious skin reactions) to meloxicam or any components of the drug product [see Warnings and Precautions (5.7, 5.9)]
- History of asthma, urticaria, or other allergic-type reactions after taking aspirin or other NSAIDs. Severe, sometimes fatal, anaphylactic reactions to NSAIDs have been reported in such patients [see Warnings and Precautions (5.7, 5.8)]
- In the setting of coronary artery bypass graft (CABG) surgery [see Warnings and Precautions (5.1)]

5 WARNINGS AND PRECAUTIONS

5.1 Cardiovascular Thrombotic Events

Clinical trials of several COX-2 selective and nonselective NSAIDs of up to three years duration have shown an increased risk of serious cardiovascular (CV) thrombotic events, including myocardial infarction (MI) and stroke, which can be fatal. Based on available data, it is unclear that the risk for CV thrombotic events is similar for all NSAIDs. The relative increase in serious CV thrombotic events over baseline conferred by NSAID use appears to be similar in those with and without known CV disease or risk factors for CV disease. However, patients with known CV disease or risk factors had a higher absolute incidence of excess serious CV thrombotic events, due to their increased baseline rate. Some observational studies found that this increased risk of serious CV thrombotic events began as early as the first weeks of treatment. The increase in CV thrombotic risk has been observed most consistently at higher doses.

To minimize the potential risk for an adverse CV event in NSAID-treated patients, use the lowest effective dose for the shortest duration possible. Physicians and patients should remain alert for the development of such events, throughout the entire treatment course, even in the absence of previous CV symptoms. Patients should be informed about the symptoms of serious CV events and the steps to take if they occur.

There is no consistent evidence that concurrent use of aspirin mitigates the increased risk of serious CV thrombotic events associated with NSAID use. The concurrent use of aspirin and an NSAID, such as meloxicam, increases the risk of serious gastrointestinal (GI) events [see Warnings and Precautions (5.2)].

Status Post Coronary Artery Bypass Graft (CABG) Surgery

Two large, controlled clinical trials of a COX-2 selective NSAID for the treatment of pain in the first 10–14 days following CABG surgery found an increased incidence of myocardial infarction and stroke. NSAIDs are contraindicated in the setting of CABG [see Contraindications (4)].

Post-MI Patients

Observational studies conducted in the Danish National Registry have demonstrated that patients treated with NSAIDs in the post-MI period were at increased risk of reinfarction, CV-related death, and all-cause mortality beginning in the first week of treatment. In this same cohort, the incidence of death in the first year post-MI was 20 per 100 person years in NSAID-treated patients compared to 12 per 100 person years in non-NSAID exposed patients. Although the absolute rate of death declined somewhat after the first year post-MI, the increased relative risk of death in NSAID users persisted over at least the next four years of follow-up.

Avoid the use of VIVLODEX in patients with a recent MI unless the benefits are expected to outweigh the risk of recurrent CV thrombotic events. If VIVLODEX is used in patients with a recent MI, monitor patients for signs of cardiac ischemia.

5.2 Gastrointestinal Bleeding, Ulceration, and Perforation

NSAIDs, including meloxicam, cause serious gastrointestinal (GI) adverse events including inflammation, bleeding, ulceration, and perforation of the esophagus, stomach, small intestine, or large intestine, which can be fatal. These serious adverse events can occur at any time, with or without warning symptoms, in patients treated with VIVLODEX. Only one in five patients who develop a serious upper GI adverse event on NSAID therapy is symptomatic. Upper GI ulcers, gross bleeding, or perforation caused by NSAIDs occurred in approximately 1% of patients treated for 3-6 months, and in about 2%-4% of patients treated for one year. However, even short-term NSAID therapy is not without risk.

Risk Factors for GI Bleeding, Ulceration, and Perforation

Patients with a prior history of peptic ulcer disease and/or GI bleeding who used NSAIDs had a greater than 10-fold increased risk for developing a GI bleed compared to patients without these risk factors. Other factors that increase the risk for GI bleeding in patients treated with NSAIDs include longer duration of NSAID therapy; concomitant use of oral corticosteroids, aspirin, anticoagulants, or selective serotonin reuptake inhibitors (SSRIs); smoking; use of alcohol; older age; and poor general health status. Most postmarketing reports of fatal GI events occurred in elderly or debilitated patients. Additionally, patients with advanced liver disease and/or coagulopathy are at increased risk for GI bleeding.

Strategies to Minimize the GI Risks in NSAID-treated patients:

- Use the lowest effective dosage for the shortest possible duration.
- Avoid administration of more than one NSAID at a time.
- Avoid use in patients at higher risk unless benefits are expected to outweigh the increased risk of bleeding. For high risk patients, as well as those with active GI bleeding, consider alternate therapies other than NSAIDs.
- Remain alert for signs and symptoms of GI ulceration and bleeding during NSAID therapy.
- If a serious GI adverse event is suspected, promptly initiate evaluation and treatment, and discontinue VIVLODEX until a serious GI adverse event is ruled out.
- In the setting of concomitant use of low-dose aspirin for cardiac prophylaxis, monitor patients more closely for evidence of GI bleeding [see Drug Interactions (7)].

5.3 Hepatotoxicity

Elevations of ALT or AST (three or more times the upper limit of normal [ULN]) have been reported in approximately 1% of NSAID-treated patients in clinical trials. In addition, rare, sometimes fatal, cases of severe hepatic injury, including fulminant hepatitis, liver necrosis, and hepatic failure have been reported.

Elevations of ALT or AST (less than three times ULN) may occur in up to 15% of patients treated with NSAIDs including meloxicam.

Inform patients of the warning signs and symptoms of hepatotoxicity (e.g., nausea, fatigue, lethargy, diarrhea, pruritus, jaundice, right upper quadrant tenderness, and "flulike" symptoms). If clinical signs and symptoms consistent with liver disease develop, or if systemic manifestations occur (e.g., eosinophilia, rash, etc.), discontinue VIVLODEX immediately, and perform a clinical evaluation of the patient.

5.4 Hypertension

NSAIDs, including VIVLODEX, can lead to new onset or worsening of pre-existing hypertension, either of which may contribute to the increased incidence of CV events. Patients taking angiotensin converting enzyme (ACE) inhibitors, thiazide diuretics, or loop diuretics may have impaired response to these therapies when taking NSAIDs [see Drug Interactions (7)].

Monitor blood pressure (BP) during the initiation of NSAID treatment and throughout the course of therapy.

5.5 Heart Failure and Edema

The Coxib and traditional NSAID Trialists’ Collaboration meta-analysis of randomized controlled trials demonstrated an approximately two-fold increase in hospitalizations for heart failure in COX-2 selective-treated patients and nonselective NSAID-treated patients compared to placebo-treated patients. In a Danish National Registry study of patients with heart failure, NSAID use increased the risk of MI, hospitalization for heart failure, and death.

Additionally, fluid retention and edema have been observed in some patients treated with NSAIDs. Use of meloxicam may blunt the CV effects of several therapeutic agents used to treat these medical conditions (e.g., diuretics, ACE inhibitors, or angiotensin receptor blockers [ARBs]) [see Drug Interactions (7)].

Avoid the use of VIVLODEX in patients with severe heart failure unless the benefits are expected to outweigh the risk of worsening heart failure. If VIVLODEX is used in patients with severe heart failure, monitor patients for signs of worsening heart failure.

5.6 Renal Toxicity and Hyperkalemia

Renal Toxicity

Long-term administration of NSAIDs has resulted in renal papillary necrosis and other renal injury. Renal toxicity has also been seen in patients in whom renal prostaglandins have a compensatory role in the maintenance of renal perfusion. In these patients, administration of an NSAID may cause a dose-dependent reduction in prostaglandin formation and, secondarily, in renal blood flow, which may precipitate overt renal decompensation. Patients at greatest risk of this reaction are those with impaired renal function, dehydration, hypovolemia, heart failure, liver dysfunction, those taking diuretics and ACE inhibitors or ARBs, and the elderly. Discontinuation of NSAID therapy was usually followed by recovery to the pretreatment state.

No information is available from controlled clinical studies regarding the use of VIVLODEX in patients with advanced renal disease. The renal effects of VIVLODEX may hasten the progression of renal dysfunction in patients with pre-existing renal disease.

Correct volume status in dehydrated or hypovolemic patients prior to initiating VIVLODEX. Monitor renal function in patients with renal or hepatic impairment, heart failure, dehydration, or hypovolemia during use of VIVLODEX [see Drug Interactions (7)]. Avoid the use of VIVLODEX in patients with advanced renal disease unless the benefits are expected to outweigh the risk of worsening renal function. If VIVLODEX is used in patients with advanced renal disease, monitor patients for signs of worsening renal function.

Hyperkalemia

Increases in serum potassium concentration, including hyperkalemia, have been reported with use of NSAIDs, even in some patients without renal impairment. In patients with normal renal function, these effects have been attributed to a hyporeninemic-hypoaldosteronism state.

5.7 Anaphylactic Reactions

Meloxicam has been associated with anaphylactic reactions in patients with and without known hypersensitivity to meloxicam and in patients with aspirin-sensitive asthma [see Contraindications (4), Warnings and Precautions (5.8)].

Seek emergency help if an anaphylactic reaction occurs.

5.8 Exacerbation of Asthma Related to Aspirin Sensitivity

A subpopulation of patients with asthma may have aspirin-sensitive asthma which may include chronic rhinosinusitis complicated by nasal polyps; severe, potentially fatal bronchospasm; and/or intolerance to aspirin and other NSAIDs. Because cross-reactivity between aspirin and other NSAIDs has been reported in such aspirin-sensitive patients, VIVLODEX is contraindicated in patients with this form of aspirin sensitivity [see Contraindications (4)]. When VIVLODEX is used in patients with preexisting asthma (without known aspirin sensitivity), monitor patients for changes in the signs and symptoms of asthma.

5.9 Serious Skin Reactions

NSAIDs, including meloxicam, can cause serious skin adverse reactions such as exfoliative dermatitis, Stevens-Johnson Syndrome (SJS), and toxic epidermal necrolysis (TEN), which can be fatal. These serious events may occur without warning. Inform patients about the signs and symptoms of serious skin reactions, and to discontinue the use of VIVLODEX at the first appearance of skin rash or any other sign of hypersensitivity. VIVLODEX is contraindicated in patients with previous serious skin reactions to NSAIDs [see Contraindications (4)].

5.10 Drug Reaction with Eosinophilia and Systemic Symptoms (DRESS)

Drug Reaction with Eosinophilia and Systemic Symptoms (DRESS) has been reported in patients taking NSAIDs such as VIVLODEX. Some of these events have been fatal or life-threatening. DRESS typically, although not exclusively, presents with fever, rash, lymphadenopathy, and/or facial swelling. Other clinical manifestations may include hepatitis, nephritis, hematological abnormalities, myocarditis, or myositis. Sometimes symptoms of DRESS may resemble an acute viral infection. Eosinophilia is often present. Because this disorder is variable in its presentation, other organ systems not noted here may be involved. It is important to note that early manifestations of hypersensitivity, such as fever or lymphadenopathy, may be present even though rash is not evident. If such signs or symptoms are present, discontinue VIVLODEX and evaluate the patient immediately.

5.11 Fetal Toxicity

Premature Closure of Fetal Ductus Arteriosus
Avoid use of NSAIDS, including VIVLODEX, in pregnant women at about 30 weeks of gestation and later. NSAIDs, including VIVLODEX, increase the risk of premature closure of the fetal ductus arteriosus at approximately this gestational age.

Oligohydramnios/Neonatal Renal Impairment
Use of NSAIDs, including VIVLODEX, at about 20 weeks gestation or later in pregnancy may cause fetal renal dysfunction leading to oligohydramnios and, in some cases, neonatal renal impairment. These adverse outcomes are seen, on average, after days to weeks of treatment, although oligohydramnios has been infrequently reported as soon as 48 hours after NSAID initiation.

Oligohydramnios is often, but not always, reversible with treatment discontinuation. Complications of prolonged oligohydramnios may, for example, include limb contractures and delayed lung maturation. In some postmarketing cases of impaired neonatal renal function, invasive procedures such as exchange transfusion or dialysis were required.

If NSAID treatment is necessary between about 20 weeks and 30 weeks gestation, limit VIVLODEX use to the lowest effective dose and shortest duration possssible. Consider ultrasound monitoring of amniotic fluid if VIVLODEX treatment extends beyond 48 hours. Discontinue VIVLODEX if oligohydramnios occurs and follow up according to clinical practice [see Use in Specific Populations (8.1)].

5.12 Hematologic Toxicity

Anemia has occurred in NSAID-treated patients. This may be due to occult or gross blood loss, fluid retention, or an incompletely described effect upon erythropoiesis. If a patient treated with VIVLODEX has any signs or symptoms of anemia, monitor hemoglobin or hematocrit.

NSAIDs, including VIVLODEX, may increase the risk of bleeding events. Concomitant use of warfarin and other anticoagulants, antiplatelet agents (e.g., aspirin), and serotonin reuptake inhibitors (SSRIs) and serotonin norepinephrine reuptake inhibitors (SNRIs) may increase this risk. Monitor these patients for signs of bleeding [see Drug Interactions (7)].

5.13 Masking of Inflammation and Fever

The pharmacological activity of VIVLODEX in reducing inflammation, and possibly fever, may diminish the utility of diagnostic signs in detecting infections.

5.14 Laboratory Monitoring

Because serious GI bleeding, hepatotoxicity, and renal injury can occur without warning symptoms or signs, consider monitoring patients on long-term NSAID treatment with a CBC and a chemistry profile periodically [see Warnings and Precautions (5.2, 5.3, 5.6)].

6 ADVERSE REACTIONS

The following adverse reactions are discussed in greater detail in other sections of the labeling:

- Cardiovascular Thrombotic Events [see Warnings and Precautions (5.1)]
- GI Bleeding, Ulceration and Perforation [see Warnings and Precautions (5.2)]
- Hepatotoxicity [see Warnings and Precautions (5.3)]
- Hypertension [see Warnings and Precautions (5.4)]
- Heart Failure and Edema [see Warnings and Precautions (5.5)]
- Renal Toxicity and Hyperkalemia [see Warnings and Precautions (5.6)]
- Anaphylactic Reactions [see Warnings and Precautions (5.7)]
- Serious Skin Reactions [see Warnings and Precautions (5.9)]
- Hematologic Toxicity [see Warnings and Precautions (5.11)]

6.1 Clinical Trials Experience

Because clinical trials are conducted under widely varying conditions, adverse reaction rates observed in the clinical trials of a drug cannot be directly compared to rates in the clinical trials of another drug and may not reflect the rates observed in practice.

Adverse Reactions in Patients with Osteoarthritis Pain

Eight hundred sixty-eight (868) patients with osteoarthritis pain, ranging in age from 40 – 87 years, were enrolled in two Phase 3 clinical trials and received VIVLODEX 5 mg or 10 mg once daily. Fifty percent (50%) of patients were aged 61 years or older.

Two hundred sixty-nine (269) patients received VIVLODEX 5 mg or 10 mg once daily in the 12-week, double-blind, placebo-controlled, clinical trial of osteoarthritis pain of the knee or hip. The most frequent adverse reactions in this study are summarized in Table 1.

Table 1 Summary of Adverse Reactions (≥2%) – 12-Week Phase 3 Study in Patients With Osteoarthritis Pain
Adverse Reactions | VIVLODEX 5 mg or 10 mg N=269 | Placebo N=133
Diarrhea | 3% | 1%
Nausea | 2% | 0
Abdominal Discomfort | 2% | 0

Six hundred (600) patients received VIVLODEX 10 mg once daily in a 52-week, open-label, clinical trial in osteoarthritis pain of the knee or hip. Of these, 390 (65%) patients completed the trial. The most frequent adverse reactions in this study are summarized in Table 2.

Table 2 Summary of Adverse Reactions (≥2%) – 52-Week Open-Label Study in Patients With Osteoarthritis Pain
Adverse Reactions | VIVLODEX 10 mg N=600
Arthralgia | 6%
Urinary Tract Infection | 6%
Osteoarthritis | 5%
Hypertension | 4%
Diarrhea | 4%
Headache | 4%
Upper Respiratory Tract Infection | 4%
Back Pain | 4%
Nasopharyngitis | 4%
Bronchitis | 3%
Sinusitis | 3%
Constipation | 3%
Dyspepsia | 3%
Nausea | 2%
Edema Peripheral | 2%
Pain in Extremity | 2%

Additional adverse reactions reported for meloxicam:

Body as a Whole | allergic reaction, face edema, fatigue, fever, hot flushes, malaise, syncope, weight decrease, weight increase
Cardiovascular | angina pectoris, cardiac failure, hypertension, hypotension, myocardial infarction, vasculitis
Central and Peripheral Nervous System | convulsions, paresthesia, tremor, vertigo
Gastrointestinal | colitis, dry mouth, duodenal ulcer, eructation, esophagitis, gastric ulcer, gastritis, gastroesophageal reflux, gastrointestinal hemorrhage, hematemesis, hemorrhagic duodenal ulcer, hemorrhagic gastric ulcer, intestinal perforation, melena, pancreatitis, perforated duodenal ulcer, perforated gastric ulcer, stomatitis ulcerative
Heart Rate and Rhythm | arrhythmia, palpitation, tachycardia
Hematologic | agranulocytosis, leukopenia, purpura, thrombocytopenia
Immune System | anaphylactoid reactions (including shock)
Liver and Biliary System | ALT increased, AST increased, bilirubinemia, GGT increased, hepatitis, jaundice, liver failure
Metabolic and Nutritional | dehydration
Psychiatric | abnormal dreaming, alterations in mood (such as mood elevation), anxiety, appetite increased, confusion, depression, nervousness, somnolence,
Respiratory | asthma, bronchospasm, dyspnea
Skin and Appendages | alopecia, angioedema, bullous eruption, erythema multiforme, exfoliative dermatitis, photosensitivity reaction, pruritus, Stevens-Johnson Syndrome, toxic epidermal necrolysis, sweating increased, urticaria
Special Senses | abnormal vision, conjunctivitis, taste perversion, tinnitus
Urinary System | albuminuria, acute urinary retention, BUN increased, creatinine increased, hematuria, interstitial nephritis, renal failure,

7 DRUG INTERACTIONS

See Table 3 for clinically significant drug interactions with meloxicam.

Table 3 Clinically Significant Drug Interactions with meloxicam
Drugs That Interfere with Hemostasis
Clinical Impact: | - Meloxicam and anticoagulants such as warfarin have a synergistic effect on bleeding. The concomitant use of meloxicam and anticoagulants have an increased risk of serious bleeding compared to the use of either drug alone. - Serotonin release by platelets plays an important role in hemostasis. Case-control and cohort epidemiological studies showed that concomitant use of drugs that interfere with serotonin reuptake and an NSAID may potentiate the risk of bleeding more than an NSAID alone.
Intervention: | Monitor patients with concomitant use of VIVLODEX with anticoagulants (e.g., warfarin), antiplatelet agents (e.g., aspirin), selective serotonin reuptake inhibitors (SSRIs), and serotonin norepinephrine reuptake inhibitors (SNRIs) for signs of bleeding [see Warnings and Precautions (5.11)].
Aspirin
Clinical Impact: | Controlled clinical studies showed that the concomitant use of NSAIDs and analgesic doses of aspirin does not produce any greater therapeutic effect than the use of NSAIDs alone. In a clinical study, the concomitant use of an NSAID and aspirin was associated with a significantly increased incidence of GI adverse reactions as compared to use of the NSAID alone [see Warnings and Precautions (5.2)].
Intervention: | Concomitant use of VIVLODEX and analgesic doses of aspirin is not generally recommended because of the increased risk of bleeding [see Warnings and Precautions (5.11)].
ACE Inhibitors, Angiotensin Receptor Blockers, and Beta-Blockers
Clinical Impact: | - NSAIDs may diminish the antihypertensive effect of angiotensin converting enzyme (ACE) inhibitors, angiotensin receptor blockers (ARBs), or beta-blockers (including propranolol). - In patients who are elderly, volume-depleted (including those on diuretic therapy), or have renal impairment, co-administration of an NSAID with ACE inhibitors or ARBs may result in deterioration of renal function, including possible acute renal failure. These effects are usually reversible.
Intervention: | - During concomitant use of VIVLODEX and ACE-inhibitors, ARBs, or beta-blockers, monitor blood pressure to ensure that the desired blood pressure is obtained. - During concomitant use of VIVLODEX and ACE-inhibitors or ARBs in patients who are elderly, volume-depleted, or have impaired renal function, monitor for signs of worsening renal function [see Warnings and Precautions (5.6)].
Diuretics
Clinical Impact: | Clinical studies, as well as post-marketing observations, showed that NSAIDs reduced the natriuretic effect of loop diuretics (e.g., furosemide) and thiazide diuretics in some patients. This effect has been attributed to the NSAID inhibition of renal prostaglandin synthesis.
Intervention: | During concomitant use of VIVLODEX with diuretics, observe patients for signs of worsening renal function, in addition to assuring diuretic efficacy including antihypertensive effects [see Warnings and Precautions (5.6)]
Digoxin
Clinical Impact: | The concomitant use of meloxicam with digoxin has been reported to increase the serum concentration and prolong the half-life of digoxin.
Intervention: | During concomitant use of VIVLODEX and digoxin, monitor serum digoxin levels.
Lithium
Clinical Impact: | NSAIDs have produced elevations in plasma lithium levels and reductions in renal lithium clearance. The mean minimum lithium concentration increased 15%, and the renal clearance decreased by approximately 20%. This effect has been attributed to NSAID inhibition of renal prostaglandin synthesis.
Intervention: | During concomitant use of VIVLODEX and lithium, monitor patients for signs of lithium toxicity.
Methotrexate
Clinical Impact: | Concomitant use of NSAIDs and methotrexate may increase the risk for methotrexate toxicity (e.g., neutropenia, thrombocytopenia, renal dysfunction).
Intervention: | During concomitant use of VIVLODEX and methotrexate, monitor patients for methotrexate toxicity.
Cyclosporine
Clinical Impact: | Concomitant use of VIVLODEX and cyclosporine may increase cyclosporine’s nephrotoxicity.
Intervention: | During concomitant use of VIVLODEX and cyclosporine, monitor patients for signs of worsening renal function.
NSAIDs and Salicylates
Clinical Impact: | Concomitant use of meloxicam with other NSAIDs or salicylates (e.g., diflunisal, salsalate) increases the risk of GI toxicity, with little or no increase in efficacy [see Warnings and Precautions(5.2)].
Intervention: | The concomitant use of meloxicam with other NSAIDs or salicylates is not recommended.
Pemetrexed
Clinical Impact: | Concomitant use of VIVLODEX and pemetrexed may increase the risk of pemetrexed-associated myelosuppression, renal, and GI toxicity (see the pemetrexed prescribing information).
Intervention: | During concomitant use of VIVLODEX and pemetrexed, in patients with renal impairment whose creatinine clearance ranges from 45 to 79 mL/min, monitor for myelosuppression, renal and GI toxicity. NSAIDs with short elimination half-lives (e.g., diclofenac, indomethacin) should be avoided for a period of two days before, the day of, and two days following administration of pemetrexed. In the absence of data regarding potential interaction between pemetrexed and NSAIDs with longer half-lives (e.g., meloxicam, nabumetone), patients taking these NSAIDs should interrupt dosing for at least five days before, the day of, and two days following pemetrexed administration.

8 USE IN SPECIFIC POPULATIONS

8.1 Pregnancy

Risk Summary

Use of NSAIDs, including VIVLODEX, can cause premature closure of the fetal ductus arteriosus and fetal renal dysfunction leading to oligohydramnios and, in some cases, neonatal renal impairment. Because of these risks, limit dose and duration of VIVLODEX use between about 20 and 30 weeks of gestation, and avoid VIVLODEX use at about 30 weeks of gestation and later in pregnancy (see Clinical Considerations, Data).

Premature Closure of Fetal Ductus Arteriosus

Use of NSAIDs, including VIVLODEX, at about 30 weeks gestation or later in
pregnancy increases the risk of premature closure of the fetal ductus arteriosus.

Oligohydramnios/Neonatal Renal Impairment

Use of NSAIDs at about 20 weeks gestation or later in pregnancy has been
associated with cases of fetal renal dysfunction leading to oligohydramnios, and in
some cases, neonatal renal impairment.

Data from observational studies regarding other potential embryofetal risks of NSAID use in women in the first or second trimesters of pregnancy are inconclusive.

In animal reproduction studies, embryofetal death was observed in rats and rabbits treated during the period of organogenesis with meloxicam at oral doses equivalent 1- and 10-times, respectively, the maximum recommended daily dose (MRDD) of VIVLODEX. Increased incidence of septal heart defects were observed in rabbits treated throughout embryogenesis with meloxicam at an oral dose equivalent to 116-times the MRDD. In pre- and post-natal reproduction studies, increased incidence of dystocia, delayed parturition, and decreased offspring survival were observed in rats treated with meloxicam at an oral dose equivalent to 0.12-times the MRDD of VIVLODEX. No teratogenic effects were observed in rats treated with meloxicam during organogenesis at an oral dose equivalent to 3.9- times the MRDD [see Data].

Based on animal data, prostaglandins have been shown to have an important role in endometrial vascular permeability, blastocyst implantation, and decidualization. In animal studies, administration of prostaglandin synthesis inhibitors such as meloxicam, resulted in increased pre- and post-implantation loss. Prostaglandins also have been shown to have an important role in fetal kidney development. In published animal studies, prostaglandin synthesis inhibitors have been reported to impair kidney development when administered at clinically relevant doses.

The estimated background risk of major birth defects and miscarriage for the indicated population(s) is unknown. All pregnancies have a background risk of birth defect, loss, or other adverse outcomes. In the U.S. general population, the estimated background risk of major birth defects and miscarriage in clinically recognized pregnancies is 2% to 4% and 15% to 20%, respectively.

Clinical Considerations

Fetal/Neonatal Adverse Reactions

Premature Closure of Fetal Ductus Arteriosus:

Avoid use of NSAIDs in women at about 30 weeks gestation and later in pregnancy,
because NSAIDs, including VIVLODEX, can cause premature closure of the fetal
ductus arteriosus (see Data).

Oligohydramnios/Neonatal Renal Impairment:

If an NSAID is necessary at about 20 weeks gestation or later in pregnancy, limit the
use to the lowest effective dose and shortest duration possible. If VIVLODEX
treatment extends beyond 48 hours, consider monitoring with ultrasound for
oligohydramnios. If oligohydramnios occurs, discontinue VIVLODEX and follow
up according to clinical practice (see Data).

Labor or Delivery

There are no studies on the effects of VIVLODEX during labor or delivery. In
animal studies, NSAIDs, including meloxicam, inhibit prostaglandin synthesis, cause
delayed parturition, and increase the incidence of stillbirth.

Data

Human Data

Premature Closure of Fetal Ductus Arteriosus:

Published literature reports that the use of NSAIDs at about 30 weeks of gestation
and later in pregnancy may cause premature closure of the fetal ductus arteriosus.

Oligohydramnios/Neonatal Renal Impairment:

Published studies and postmarketing reports describe maternal NSAID use at about
20 weeks gestation or later in pregnancy associated with fetal renal dysfunction
leading to oligohydramnios, and in some cases, neonatal renal impairment. These
adverse outcomes are seen, on average, after days to weeks of treatment, although
oligohydramnios has been infrequently reported as soon as 48 hours after NSAID
initiation. In many cases, but not all, the decrease in amniotic fluid was transient and
reversible with cessation of the drug. There have been a limited number of case
reports of maternal NSAID use and neonatal renal dysfunction without
oligohydramnios, some of which were irreversible. Some cases of neonatal renal
dysfunction required treatment with invasive procedures, such as exchange
transfusion or dialysis.

Methodological limitations of these postmarketing studies and reports include lack
of a control group; limited information regarding dose, duration, and timing of drug
exposure; and concomitant use of other medications. These limitations preclude
establishing a reliable estimate of the risk of adverse fetal and neonatal outcomes
with maternal NSAID use. Because the published safety data on neonatal outcomes
involved mostly preterm infants, the generalizability of certain reported risks to the
full-term infant exposed to NSAIDs through maternal use is uncertain.

Animal data
Meloxicam was not teratogenic when administered to pregnant rats during fetal
organogenesis at oral doses up to 4 mg/kg/day (3.9-times the maximum recommended
daily dose (MRDD) of 10 mg of VIVLODEX based on body surface area [BSA]
comparison). Administration of meloxicam to pregnant rabbits throughout
embryogenesis produced an increased incidence of septal defects of the heart at an
oral dose of 60 mg/kg/day (116-times the MRDD based on BSA comparison). The no
effect level was 20 mg/kg/day (39-times the MRDD based on BSA comparison). In
rats and rabbits, embryolethality occurred at oral meloxicam doses of 1 mg/kg/day
and 5 mg/kg/day, respectively (1- and 10-times the MRDD based on BSA
comparison) when administered throughout organogenesis.

Oral administration of meloxicam to pregnant rats during late gestation through
lactation increased the incidence of dystocia, delayed parturition, and decreased
offspring survival at meloxicam doses of 0.125 mg/kg/day or greater (0.12-times the
MRDD based on BSA comparison).

8.2 Lactation

Risk Summary

There are no human data available on whether meloxicam is present in human milk, or on the effects on breastfed infants, or on milk production. The developmental and health benefits of breastfeeding should be considered along with the mother’s clinical need for VIVLODEX and any potential adverse effects on the breastfed infant from the VIVLODEX or from the underlying maternal condition.

Data

Animal data

Meloxicam was excreted in the milk of lactating rats at concentrations higher than those in plasma.

8.3 Females and Males of Reproductive Potential

Infertility

Females

Based on the mechanism of action, the use of prostaglandin-mediated NSAIDs, including VIVLODEX, may delay or prevent rupture of ovarian follicles, which has been associated with reversible infertility in some women. Published animal studies have shown that administration of prostaglandin synthesis inhibitors has the potential to disrupt prostaglandin-mediated follicular rupture required for ovulation. Small studies in women treated with NSAIDs have also shown a reversible delay in ovulation. Consider withdrawal of NSAIDs, including VIVLODEX, in women who have difficulties conceiving or who are undergoing investigation of infertility.

8.4 Pediatric Use

The safety and effectiveness of VIVLODEX in pediatric patients has not been established.

8.5 Geriatric Use

Elderly patients, compared to younger patients, are at greater risk for NSAID-associated serious cardiovascular, gastrointestinal, and/or renal adverse reactions. If the anticipated benefit for the elderly patient outweighs these potential risks, start dosing at the low end of the dosing range, and monitor patients for adverse effects [see Warnings and Precautions (5.1, 5.2, 5.3, 5.6, 5.13)]. Of the total number of patients in clinical studies of VIVLODEX, 291 were age 65 and over. No overall differences in safety or effectiveness were observed between these subjects and younger subjects, and other reported clinical experience has not identified differences in responses between the elderly and younger patients, but greater sensitivity of some older individuals cannot be ruled out.

8.6 Hepatic Impairment

No dose adjustment is necessary in patients with mild to moderate hepatic impairment. Patients with severe hepatic impairment have not been adequately studied. Because meloxicam is significantly metabolized in the liver; use VIVLODEX in patients with severe hepatic impairment only if the benefits are expected to outweigh the risks. If VIVLODEX is used in patients with severe hepatic impairment, monitor patients for signs of worsening liver function [see Warnings and Precautions (5.3), Clinical Pharmacology (12.3)].

8.7 Renal Impairment

No dose adjustment is necessary in patients with mild to moderate renal impairment. Patients with severe renal impairment have not been studied. The use of VIVLODEX in subjects with severe renal impairment is not recommended. In a previous study, the free Cmax plasma concentrations following a single dose of meloxicam were higher in patients with renal failure on chronic hemodialysis (1% free fraction) in comparison to healthy volunteers (0.3% free fraction). Therefore, the maximum VIVLODEX dosage in this population is 5 mg per day. Hemodialysis did not lower the total drug concentration in plasma; therefore, additional doses are not necessary after hemodialysis. Meloxicam is not dialyzable [see Warnings and Precautions (5.6), Clinical Pharmacology (12.3)].

10 OVERDOSAGE

Symptoms following acute NSAID overdosages have been typically limited to lethargy, drowsiness, nausea, vomiting, and epigastric pain, which have been generally reversible with supportive care. Gastrointestinal bleeding has occurred. Hypertension, acute renal failure, respiratory depression, and coma have occurred, but were rare [see Warnings and Precautions (5.1, 5.2)].

There is limited experience with meloxicam overdose. In four reported cases of meloxicam overdose, patients took 6 to 11 times the highest available dose of meloxicam tablets (15 mg); all recovered. Cholestyramine is known to accelerate the clearance of meloxicam.

Manage patients with symptomatic and supportive care following an NSAID overdosage. There are no specific antidotes. Consider emesis and/or activated charcoal (60 to 100 grams in adults, 1 to 2 grams per kg of body weight in pediatric patients) and/or osmotic cathartic in symptomatic patients seen within four hours of ingestion or in patients with a large overdosage (5 to 10 times the recommended dosage). Accelerated removal of meloxicam by 4 g oral doses of cholestyramine given three times a day was demonstrated in a previous clinical trial. Forced diuresis, alkalinization of urine, hemodialysis, or hemoperfusion may not be useful due to high protein binding.

For additional information about overdosage treatment contact a poison control center (1-800-222-1222).

11 DESCRIPTION

VIVLODEX (meloxicam) capsules are a nonsteroidal anti-inflammatory drug, available as pink and blue capsules containing 5 mg or 10 mg for oral administration. The chemical name is 4 hydroxy-2-methyl-N-(5-methyl-2-thiazolyl)-2H-1,2-benzothiazine-3-carboxamide-1, 1-dioxide. The molecular weight is 351.4. Its molecular formula is C14H13N3O4S2, and it has the following chemical structure.

Meloxicam is a pale yellow solid, practically insoluble in water, with higher solubility observed in strong acids and bases. It is very slightly soluble in methanol. Meloxicam has an apparent partition coefficient (log P)app=0.1 in n-octanol/buffer pH 7.4. Meloxicam has pKa values of 1.1 and 4.2.

The inactive ingredients in VIVLODEX include: lactose monohydrate, sodium lauryl sulfate, sodium stearyl fumarate, microcrystalline cellulose, and croscarmellose sodium. The capsule shells contain gelatin, titanium dioxide, and dyes FD&C blue #2, FD&C red #40, FD&C yellow #6, and carmine. The imprinting on the gelatin capsules is white edible ink. The 5 mg capsules have a light pink body with “IP-205” imprinted in white ink and a dark blue cap with “5 mg” imprinted in white ink. The 10 mg capsules have a pink body with “IP-206” imprinted in white ink and a dark blue cap with “10 mg” imprinted in white ink.

12 CLINICAL PHARMACOLOGY

12.1 Mechanism of Action

VIVLODEX has analgesic, anti-inflammatory, and antipyretic properties.

The mechanism of action of VIVLODEX, like that of other NSAIDs, is not completely understood but involves inhibition of cyclooxygenase (COX-1 and COX-2).

Meloxicam is a potent inhibitor of prostaglandin synthesis in vitro. Meloxicam concentrations reached during therapy have produced in vivo effects. Prostaglandins sensitize afferent nerves and potentiate the action of bradykinin in inducing pain in animal models. Prostaglandins are mediators of inflammation. Because meloxicam is an inhibitor of prostaglandin synthesis, its mode of action may be due to a decrease of prostaglandins in peripheral tissues.

12.3 Pharmacokinetics

The relative bioavailability of VIVLODEX 10 mg capsules compared to meloxicam 15 mg tablets was assessed in 28 healthy subjects under fasted and fed conditions in a single-dose crossover study.

VIVLODEX 10 mg capsules do not result in an equivalent systemic exposure compared to 15 mg meloxicam tablets. When taken under fasted conditions, a 33% lower dose of meloxicam in VIVLODEX 10 mg capsules resulted in a 33% lower overall systemic exposure (AUCinf) and a comparable mean peak plasma concentration (Cmax) to meloxicam 15 mg tablets. The median time to maximum plasma concentration (Tmax) occurred earlier for VIVLODEX capsules (2 hours for both 5 mg and 10 mg) than for meloxicam tablets (4 hours for 15 mg).

Absorption

Single oral doses of VIVLODEX 5 mg and 10 mg were associated with dose-proportional pharmacokinetics. Mean Cmax was achieved within 2 hours post-dose for both VIVLODEX 5 mg and 10 mg capsules when taken under fasted conditions. A second meloxicam concentration peak occurs around 8 hours post-dose.

Taking VIVLODEX with food causes a decrease in the rate but not the overall extent of systemic meloxicam absorption compared with taking VIVLODEX on an empty stomach. VIVLODEX capsules administered under fed conditions results in 22% lower mean Cmax and a 3 hour delay in median Tmax (5 hours for fed versus 2 hours for fasted) compared to the fasted condition. Significant changes in AUCinf were not observed. VIVLODEX can be administered without regard to timing of meals.

Distribution

The mean volume of distribution (Vss) of meloxicam is approximately 10 L. Meloxicam is ~99.4% bound to human plasma proteins (primarily albumin) within the therapeutic dose range. The fraction of protein binding is independent of drug concentration, over the clinically relevant concentration range, but decreases to ~99% in patients with renal disease. Meloxicam penetration into human red blood cells, after oral dosing, is less than 10%. Following a radiolabeled dose, over 90% of the radioactivity detected in the plasma was present as unchanged meloxicam.

Meloxicam concentrations in synovial fluid, after a single oral dose, range from 40% to 50% of those in plasma. The free fraction in synovial fluid is 2.5 times higher than in plasma, due to the lower albumin content in synovial fluid as compared to plasma. The significance of this penetration is unknown.

Elimination

Metabolism

Meloxicam is extensively metabolized in the liver. Meloxicam metabolites include 5'-carboxy meloxicam (60% of dose), from P-450 mediated metabolism formed by oxidation of an intermediate metabolite 5'-hydroxymethyl meloxicam which is also excreted to a lesser extent (9% of dose). In vitro studies indicate that CYP2C9 (cytochrome P450 metabolizing enzyme) plays an important role in this metabolic pathway with a minor contribution of the CYP3A4 isozyme. Patients’ peroxidase activity is probably responsible for the other two metabolites which account for 16% and 4% of the administered dose, respectively. The four metabolites are not known to have any in vivo pharmacological activity.

Excretion

Meloxicam excretion is predominantly in the form of metabolites, and occurs to equal extents in the urine and feces. Only traces of the unchanged parent compound are excreted in the urine (0.2%) and feces (1.6%). The extent of the urinary excretion was confirmed for unlabeled multiple 7.5 mg doses: 0.5%, 6%, and 13% of the dose were found in urine in the form of meloxicam, and the 5'-hydroxymethyl and 5'-carboxy metabolites, respectively. There is significant biliary and/or enteral secretion of the drug. This was demonstrated when oral administration of cholestyramine following a single IV dose of meloxicam decreased the AUC of meloxicam by 50%.

The mean elimination half-life (t1/2) for VIVLODEX 5 mg and 10 mg is approximately 22 hours.

Specific Populations

Pediatric: The pharmacokinetics of VIVLODEX have not been investigated in pediatric patients.

Hepatic Impairment: Following a single 15 mg dose of meloxicam tablets there was no marked difference in plasma concentrations in patients with mild (Child-Pugh Class I) or moderate (Child-Pugh Class II) hepatic impairment compared to healthy volunteers. Protein binding of meloxicam was not affected by hepatic impairment. No dosage adjustment is necessary in patients with mild to moderate hepatic impairment. Patients with severe hepatic impairment (Child-Pugh Class III) have not been adequately studied [see Warnings and Precautions (5.3), Use in Specific Populations (8.6)].

Renal Impairment: Meloxicam pharmacokinetics have been investigated in subjects with mild and moderate renal impairment. Total drug plasma concentrations of meloxicam decreased and total clearance of meloxicam increased with the degree of renal impairment while free AUC values were similar in all groups. The higher meloxicam clearance in subjects with renal impairment may be due to increased fraction of unbound meloxicam which is available for hepatic metabolism and subsequent excretion. No dosage adjustment is necessary in patients with mild to moderate renal impairment. Patients with severe renal impairment have not been adequately studied. The use of VIVLODEX in subjects with severe renal impairment is not recommended.

Following a single dose of meloxicam, the free Cmax plasma concentrations were higher in patients with renal failure on chronic hemodialysis (1% free fraction) in comparison to healthy volunteers (0.3% free fraction). Hemodialysis did not lower the total drug concentration in plasma; therefore, additional doses are not necessary after hemodialysis. Meloxicam is not dialyzable [see Warnings and Precautions (5.6), Use in Specific Populations (8.7)].

Drug Interaction Studies

Aspirin: When NSAIDs were administered with aspirin, the protein binding of NSAIDs were reduced, although the clearance of free NSAID was not altered. The clinical significance of this interaction is not known. See Table 3 clinically significant drug interactions of NSAIDs with aspirin [see Drug Interactions (7)].

Cholestyramine: Pretreatment for four days with cholestyramine significantly increased the clearance of meloxicam by 50%. This resulted in a decrease in t1/2, from 19.2 hours to 12.5 hours, and a 35% reduction in AUC. This suggests the existence of a recirculation pathway for meloxicam in the gastrointestinal tract. The clinical relevance of this interaction has not been established.

Cimetidine: Concomitant administration of 200 mg cimetidine four times daily did not alter the single-dose pharmacokinetics of 30 mg meloxicam.

Digoxin: Meloxicam tablets 15 mg once daily for 7 days did not alter the plasma concentration profile of digoxin after β-acetyldigoxin administration for 7 days at clinical doses. In vitro testing found no protein binding drug interaction between digoxin and meloxicam [see Drug Interactions (7)].

Lithium: In a study conducted in healthy subjects, mean pre-dose lithium concentration and AUC were increased by 21% in subjects receiving lithium doses ranging from 804 to 1072 mg twice daily with meloxicam tablets 15 mg once per day every day as compared to subjects receiving lithium alone [see Drug Interactions (7)].

Methotrexate: A previous study in 13 rheumatoid arthritis (RA) patients evaluated the effects of multiple doses of meloxicam on the pharmacokinetics of methotrexate taken once weekly. Meloxicam did not have a significant effect on the pharmacokinetics of single doses of methotrexate. In vitro, methotrexate did not displace meloxicam from its human serum binding sites [see Drug Interactions (7)].

Warfarin: The effect of meloxicam tablets on the anticoagulant effect of warfarin was studied in a group of healthy subjects receiving daily doses of warfarin that produced an INR (International Normalized Ratio) between 1.2 and 1.8. In these subjects, meloxicam did not alter warfarin pharmacokinetics and the average anticoagulant effect of warfarin as determined by prothrombin time. However, one subject showed an increase in INR from 1.5 to 2.1. Caution should be used when administering VIVLODEX with warfarin since patients on warfarin may experience changes in INR and an increased risk of bleeding complications when a new medication is introduced [see Drug Interactions (7)].

13 NONCLINICAL TOXICOLOGY

13.1 Carcinogenesis, Mutagenesis, and Impairment of Fertility

Carcinogenesis

There was no increase in tumor incidence in long-term carcinogenicity studies in rats (104 weeks) and mice (99 weeks) administered meloxicam at oral doses up to 0.8 mg/kg/day in rats and up to 8.0 mg/kg/day in mice (up to 0.8- and 3.9-times, respectively, the maximum recommended daily dose (MRDD) of 10 mg of VIVLODEX based on body surface area (BSA) comparison).

Mutagenesis

Meloxicam was not mutagenic in an Ames assay, or clastogenic in a chromosome aberration assay with human lymphocytes and an in vivo micronucleus test in mouse bone marrow.

Impairment of Fertility

In previous studies of meloxicam, there was no impairment of male or female fertility in rats at oral doses up to 9 mg/kg/day in males and 5 mg/kg/day in females (up to 8.7 and 4.8-times, respectively, the MRDD based on BSA comparison).

14 CLINICAL STUDIES

14.1 Osteoarthritis Pain

The efficacy of VIVLODEX in the management of osteoarthritis pain was demonstrated in a randomized, double-blind, multicenter, parallel-arm, placebo-controlled study comparing VIVLODEX 5 mg or 10 mg taken once daily and placebo in patients with pain due to osteoarthritis of the knee or hip. The study evaluated 402 patients with a mean age of 61 (range 40 to 87 years). Osteoarthritis pain was measured using the Western Ontario and McMaster University Osteoarthritis Index (WOMAC) Pain Subscale. The mean baseline WOMAC Pain Subscale Score across treatment groups was 73 mm using a 0 to 100 mm visual analog scale.

The primary efficacy endpoint was the change from baseline to Week 12 in the WOMAC Pain Subscale Score. VIVLODEX 5 mg and 10 mg once daily significantly reduced osteoarthritis pain compared with placebo, as measured by changes in WOMAC Pain Subscale Scores. Although both the 5 mg and 10 mg doses significantly reduced pain compared to placebo, the proportion of responders achieving various percentage reductions in pain intensity from baseline to Week 12 is similar for both the 5 mg and 10 mg once daily doses. The proportion (%) of patients in each group who demonstrated reduction in their pain intensity score from baseline to Week 12 is shown in Figure 1. The figure is cumulative, so patients whose change from baseline is, for example, 30%, are also included in every level of pain reduction below 30%. Patients who did not complete the study were classified as non-responders.

Figure 1 Proportion (%) of Patients Achieving Various Percentage Reductions in Pain Intensity from Baseline to Week 12

16 HOW SUPPLIED/STORAGE AND HANDLING

VIVLODEX (meloxicam) capsules are supplied as:

- 5 mg - light pink body and dark blue cap (imprinted IP-205 on the body and 5 mg on the cap in white ink)
  NDC (69344-205-23), Bottles of 30 capsules
- 10 mg - pink body and dark blue cap (imprinted IP-206 on the body and 10 mg on the cap in white ink)
  NDC (69344-206-23), Bottles of 30 capsules

Storage

Store at 25°C (77°F); excursions permitted between 15°C to 30°C (59°F to 86°F) [see USP Controlled Room Temperature].

Store in the original container and keep the bottle tightly closed to protect from moisture. Dispense in a tight container if package is subdivided.

17 PATIENT COUNSELING INFORMATION

Advise the patient to read the FDA-approved patient labeling (Medication Guide) that accompanies each prescription dispensed. Patients, families, or their caregivers should be informed of the following information before initiating therapy with VIVLODEX and periodically during the course of ongoing therapy.

Cardiovascular Thrombotic Events

Advise patients to be alert for the symptoms of cardiovascular thrombotic events, including chest pain, shortness of breath, weakness, or slurring of speech, and to report any of these symptoms to their health care provider immediately [see Warnings and Precautions (5.1)].

Gastrointestinal Bleeding, Ulceration, and Perforation

Advise patients to report symptoms of ulcerations and bleeding, including epigastric pain, dyspepsia, melena, and hematemesis to their health care provider. In the setting of concomitant use of low-dose aspirin for cardiac prophylaxis, inform patients of the increased risk for and the signs and symptoms of GI bleeding [see Warnings and Precautions (5.2)].

Hepatotoxicity

Inform patients of the warning signs and symptoms of hepatotoxicity (e.g., nausea, fatigue, lethargy, pruritus, diarrhea, jaundice, right upper quadrant tenderness, and “flu-like” symptoms). If these occur, instruct patients to stop VIVLODEX and seek immediate medical therapy [see Warnings and Precautions (5.3)].

Heart Failure and Edema

Advise patients to be alert for the symptoms of congestive heart failure including shortness of breath, unexplained weight gain, or edema and to contact their healthcare provider if such symptoms occur [see Warnings and Precautions (5.5)].

Anaphylactic Reactions

Inform patients of the signs of an anaphylactic reaction (e.g., difficulty breathing, swelling of the face or throat). Instruct patients to seek immediate emergency help if these occur [see Contraindications (4), Warnings and Precautions (5.7)].

Serious Skin Reactions, including DRESS

Advise patients to stop taking VIVLODEX immediately if they develop any type of rash or fever and to contact their healthcare provider as soon as possible [see Warnings and Precautions (5.9), (5.10)].

Fetal Toxicity

Inform pregnant women to avoid use of VIVLODEX and other NSAIDs starting at 30 weeks gestation because of the risk of the premature closing of the fetal ductus arteriosus. If treatment with VIVLODEX is needed for a pregnant woman between about 20 to 30 weeks gestation, advise her that she may need to be monitored for oligohydramnios, if treatment continues for longer than 48 hours [see Warnings and Precautions (5.10), Use in Specific Populations (8.1)].

Avoid Concomitant Use of NSAIDs

Inform patients that the concomitant use of VIVLODEX with other NSAIDs or salicylates (e.g., diflunisal, salsalate) is not recommended due to the increased risk of gastrointestinal toxicity, and little or no increase in efficacy [see Warnings and Precautions (5.2), Drug Interactions (7)]. Alert patients that NSAIDs may be present in “over the counter” medications for treatment of colds, fever, or insomnia.

Use of NSAIDs and Low-Dose Aspirin

Inform patients not to use low-dose aspirin concomitantly with VIVLODEX until they talk to their healthcare provider [see Drug Interactions (7)].

Manufactured (under license from iCeutica Pty Ltd.) for and Distributed by:
Egalet US Inc., Wayne PA 19087

©2019 Egalet Corporation. All rights reserved.US Patent Nos. 9526734, 9649318, 9808468

LBL# 701.00

Medication Guide for Nonsteroidal Anti-inflammatory Drugs (NSAIDs)

What is the most important information I should know about medicines called Nonsteroidal Anti-inflammatory Drugs (NSAIDs)?

NSAIDs can cause serious side effects, including:

- Increased risk of a heart attack or stroke that can lead to death.. This risk may happen early in treatment and may increase:
  - with increasing doses of NSAIDs
  - with longer use of NSAIDs
  Do not take NSAIDs right before or after a heart surgery called a “coronary artery bypass graft (CABG)."
  Avoid taking NSAIDs after a recent heart attack, unless your healthcare provider tells you to. You may have an increased risk of another heart attack if you take NSAIDs after a recent heart attack.
- Increased risk of bleeding, ulcers, and tears (perforation) of the esophagus (tube leading from the mouth to the stomach), stomach and intestines:
  - anytime during use
  - without warning symptoms
  - that may cause death
  The risk of getting an ulcer or bleeding increases with:
  - past history of stomach ulcers, or stomach or intestinal bleeding with use of NSAIDs
  - taking medicines called “corticosteroids”, “anticoagulants”, “SSRIs”, or “SNRIs”
  - increasing doses of NSAIDs
  - longer use of NSAIDs
  - smoking
  - drinking alcohol
  - older age
  - poor health
  - advanced liver disease
  - bleeding problems
  NSAIDs should only be used:
  - exactly as prescribed
  - at the lowest dose possible for your treatment
  - for the shortest time needed

What are NSAIDs?
NSAIDs are used to treat pain and redness, swelling, and heat (inflammation) from medical conditions such as different types of arthritis, menstrual cramps, and other types of short-term pain.

Who should not take NSAIDs?
Do not take NSAIDs:

- if you have had an asthma attack, hives, or other allergic reaction with aspirin or any other NSAIDs.
- right before or after heart bypass surgery.

Before taking NSAIDs, tell your healthcare provider about all of your medical conditions, including if you:

- have liver or kidney problems
- have high blood pressure
- have asthma
- are pregnant or plan to become pregnant. Talk to your healthcare provider if you are considering taking NSAIDs during pregnancy. You should not take NSAIDs after 29 weeks of pregnancy.
- are breastfeeding or plan to breast feed.

Tell your healthcare provider about all of the medicines you take, including prescription or over-the- counter medicines, vitamins or herbal supplements. NSAIDs and some other medicines can interact with each other and cause serious side effects. Do not start taking any new medicine without talking to your healthcare provider first.

What are the possible side effects of NSAIDs?
NSAIDs can cause serious side effects, including:

See “What is the most important information I should know about medicines called Nonsteroidal Anti- inflammatory Drugs (NSAIDs)?”

- new or worse high blood pressure
- heart failure
- liver problems including liver failure
- kidney problems including kidney failure
- low red blood cells (anemia)
- life-threatening skin reactions
- life-threatening allergic reactions
- Other side effects of NSAIDs include: stomach pain, constipation, diarrhea, gas, heartburn, nausea, vomiting, and dizziness.

Get emergency help right away if you get any of the following symptoms:

- shortness of breath or trouble breathing
- chest pain
- weakness in one part or side of your body
- slurred speech
- swelling of the face or throat

Stop taking your NSAID and call your healthcare provider right away if you get any of the following symptoms:

- nausea
- more tired or weaker than usual
- diarrhea
- itching
- your skin or eyes look yellow
- indigestion or stomach pain
- flu-like symptoms
- vomit blood
- there is blood in your bowel movement or it is black and sticky like tar
- unusual weight gain
- skin rash or blisters with fever
- swelling of the arms, legs, hands and feet

If you take too much of your NSAID, call your healthcare provider or get medical help right away.
These are not all the possible side effects of NSAIDs. For more information, ask your healthcare provider or pharmacist about NSAIDs.

Call your doctor for medical advice about side effects. You may report side effects to FDA at 1-800-FDA-1088.

Other information about NSAIDs

- Aspirin is an NSAID but it does not increase the chance of a heart attack. Aspirin can cause bleeding in the brain, stomach, and intestines. Aspirin can also cause ulcers in the stomach and intestines.
- Some NSAIDs are sold in lower doses without a prescription (over-the-counter). Talk to your healthcare provider before using over-the-counter NSAIDs for more than 10 days.

General information about the safe and effective use of NSAIDs
Medicines are sometimes prescribed for purposes other than those listed in a Medication Guide. Do not use NSAIDs for a condition for which it was not prescribed. Do not give NSAIDs to other people, even if they have the same symptoms that you have. It may harm them.

If you would like more information about NSAIDs, talk with your healthcare provider. You can ask your pharmacist or healthcare provider for information about NSAIDs that is written for health professionals.

Distributed by: Egalet US Inc., Wayne, PA 19087

For more information, go to WWW.VIVLODEX.COM or call 1-800-518-1084

This Medication Guide has been approved by the U.S. Food and Drug Administration.

Revised: 04/2021